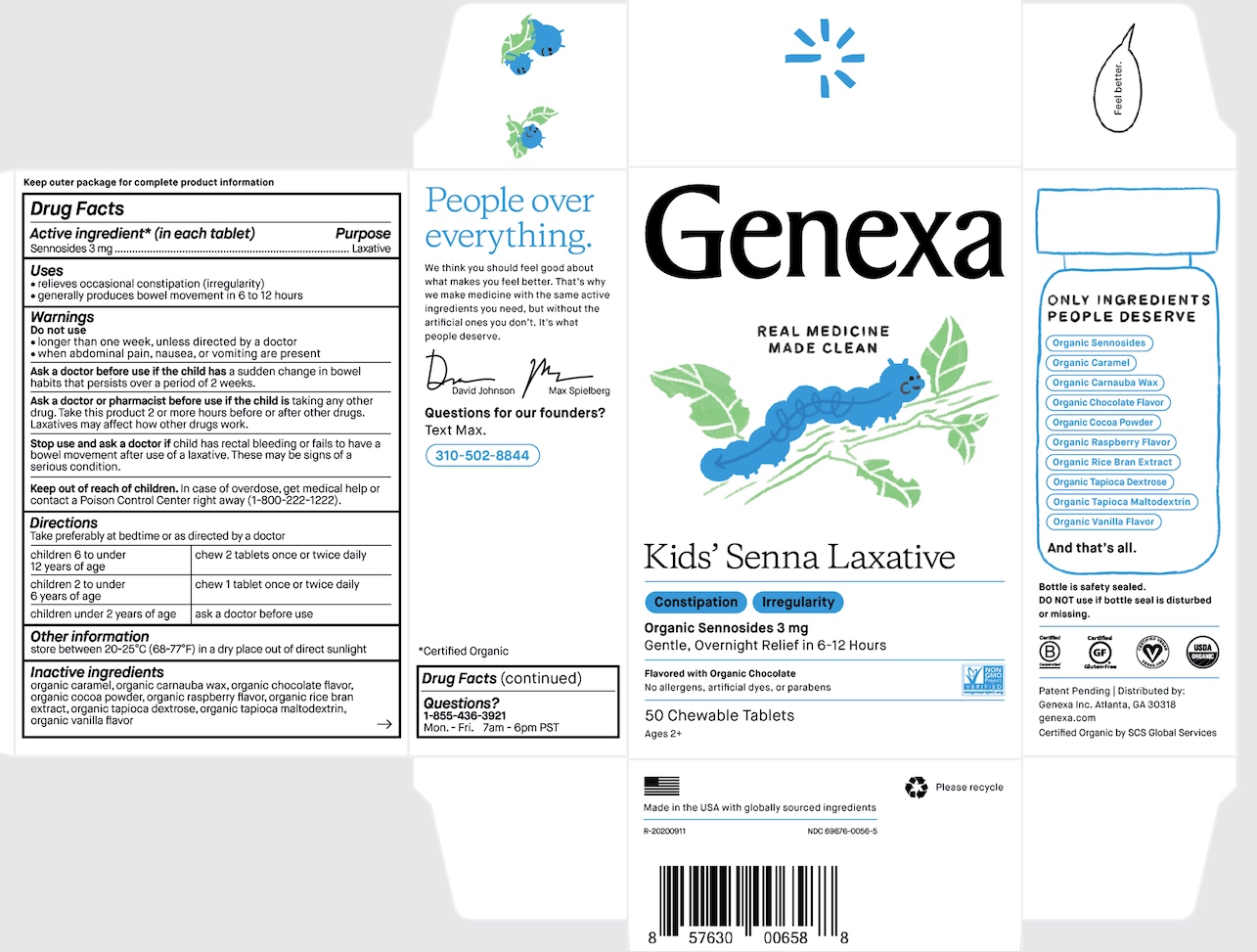 DRUG LABEL: Genexa Kids Senna Laxative
NDC: 69676-0056 | Form: TABLET, CHEWABLE
Manufacturer: Genexa Inc.
Category: otc | Type: HUMAN OTC DRUG LABEL
Date: 20230120

ACTIVE INGREDIENTS: SENNOSIDES 3 mg/1 1
INACTIVE INGREDIENTS: CARAMEL; CARNAUBA WAX; COCOA; DEXTROSE; MALTODEXTRIN; RICE BRAN

Kids' Senna Laxative

Keep outer package for complete product information

Drug Facts

Active ingredient* (in each tablet)

Sennosides 3 mg

Purpose

Laxative

Uses

- relieves occasional constipation (irregularity)
- generally produces bowel movement in 6 to 12 hours

Warnings

Do not use

- longer than one week, unless directed by a doctor
- when abdominal pain, nausea or vomiting are present

Ask a doctor before use if the child has a sudden change in bowel habits that persists over a period of 2 weeks.

Ask a doctor or pharmacist before use if the child is taking any other drug. Take this product 2 or more hours before or after other drugs. Laxatives may affect how other drugs work.

Stop use and ask a doctor if child has rectal bleeding or fails to have a bowel movement after use of a laxative. These may be signs of a serious conditon.

Keep out of reach of children. In case of overdose, get medical help or contact a Poison Control Center right away (1-800-222-1222).

Directions

Take preferably at bedtime or as directed by a doctor.

children 6 to under 12 years of age | chew 2 tablets once or twice daily
children 2 to under 6 years of age | chew 1 tablet once or twice daily
children under 2 years of age | ask a doctor before use

Other information

store between 20-25°C (68-77°F) in a dry place out of direct sunlight

INACTIVE INGREDIENT

Inactive ingredients organic caramel, organic carnauba wax, organic chocolate flavor, organic cocoa powder, organic raspberry flavor, organic rice bran extract, organic tapioca dextrose, organic tapioca maltodextrin, organic vanilla flavor

Questions?

1-855-436-3921

Mon.-Fri. 7am - 6pm PST

Bottle is safety sealed. DO NOT use if bottle seal is disturbed or missing.

Patent Pending | Distributed by:

Genexa Inc. Atlanta, GA 30318

genexa.com

Certified Organic by SCS Global Services

Made in the USA with globally sourced ingredients

R-20200911

NDC 69676-0056-5

PACKAGE LABEL

Genexa

REAL MEDICINE MADE CLEAN

Kids' Senna Laxative

Constipation Irregularity

Organic Sennosides 3 mg

Gentle, Overnight Relief in 6-12 hours

Flavored with Organic Chocolate

No allergens, artificial dyes, or parabens

50 Chewable Tablets

Ages 2+